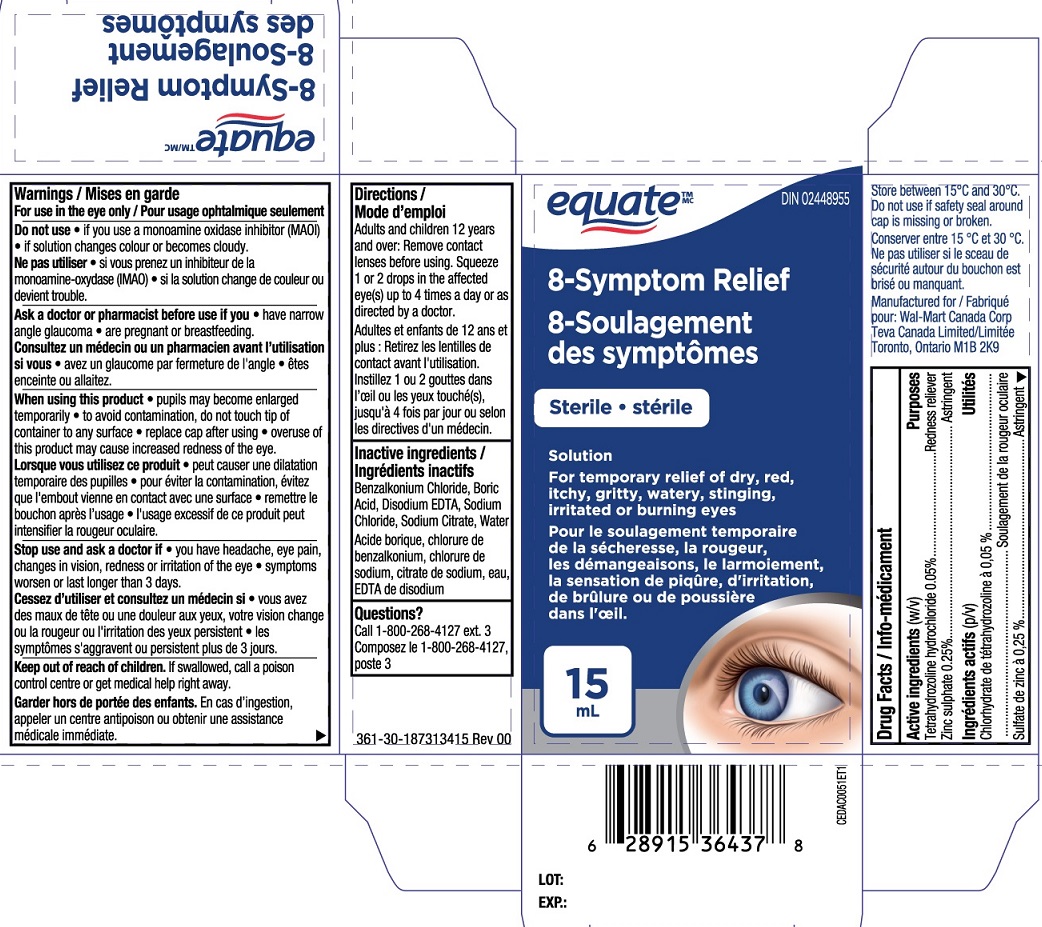 DRUG LABEL: Equate 8-symptom Relief
NDC: 55651-041 | Form: SOLUTION
Manufacturer: KC Pharmaceuticals, Inc.
Category: otc | Type: HUMAN OTC DRUG LABEL
Date: 20230323

ACTIVE INGREDIENTS: TETRAHYDROZOLINE HYDROCHLORIDE 0.05 g/100 mL; ZINC SULFATE 0.25 g/100 mL
INACTIVE INGREDIENTS: BENZALKONIUM CHLORIDE; WATER; EDETATE DISODIUM; SODIUM CHLORIDE; SODIUM CITRATE; BORIC ACID

Equate 8-symptom Relief 15 mL MFR